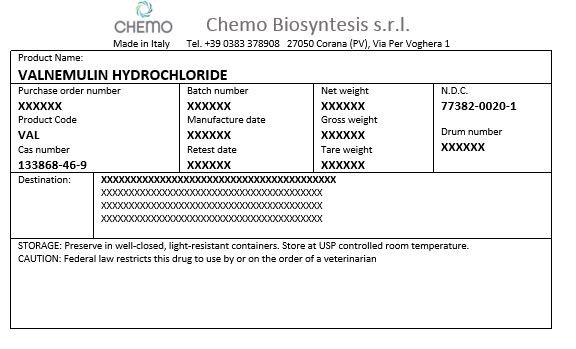 DRUG LABEL: Valnemulin Hydrochloride
NDC: 77382-0020 | Form: POWDER
Manufacturer: Chemo Biosynthesis s.r.l.
Category: other | Type: BULK INGREDIENT - ANIMAL DRUG
Date: 20220615

ACTIVE INGREDIENTS: VALNEMULIN HYDROCHLORIDE 1 kg/1 kg

PACKAGE LABEL

Valnemulin Hydrochloride